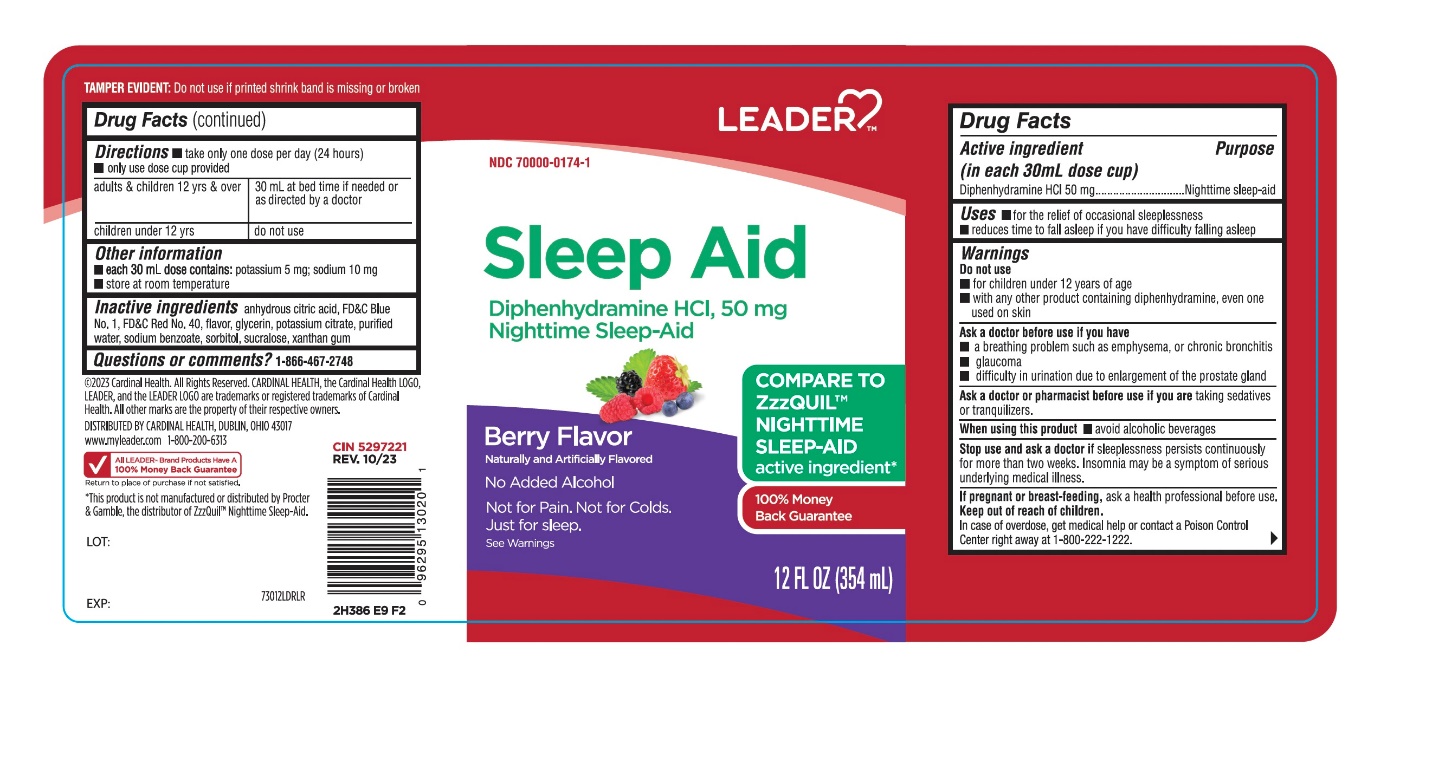 DRUG LABEL: LEADER Nighttime Sleep-Aid
NDC: 70000-0174 | Form: LIQUID
Manufacturer: CARDINAL HEALTH
Category: otc | Type: HUMAN OTC DRUG LABEL
Date: 20251014

ACTIVE INGREDIENTS: DIPHENHYDRAMINE HYDROCHLORIDE 50 mg/30 mL
INACTIVE INGREDIENTS: ANHYDROUS CITRIC ACID; FD&C BLUE NO. 1; FD&C RED NO. 40; GLYCERIN; POTASSIUM CITRATE; WATER; SODIUM BENZOATE; SORBITOL; SUCRALOSE; XANTHAN GUM

Leader Nighttime Sleep Aid Diphenhydramine HCl Berry Flavor 12 FL OZ 354mL

Drug Facts

Active ingredient (in each 30 mL dose cup)

Diphenhydramine HCl 50 mg

Purpose

Nighttime sleep-aid

Uses

- for the relief of occasional sleeplessness
- reduces time to fall asleep if you have difficulty falling asleep

Warnings

Do not use

- for children under 12 years of age
- with any other product containing diphenhydramine, even one used on skin
- with other drugs that cause drowsiness such as antihistamines and nighttime cold/flu products

Ask a doctor before use if you have

- a breathing problem such as asthma, emphysema, or chronic bronchitis
- glaucoma
- difficulty in urination due to enlargement of the prostate gland
- heart disease

Ask a doctor or pharmacist before use if you aretaking sedatives or tranquilizers or any other sleep- aid.

When using this product

- avoid alcoholic beverages and other drugs that cause drowsiness
- drowsiness will occur
- be careful when driving a motor vehicle or operating machinery

Stop use and ask a doctor ifsleeplessness persists continuously for more than two weeks. Insomnia may be a symptom of serious underlying medical illness.

PREGNANCY OR BREAST FEEDING

If pregnant or breast-feeding, ask a health professional before use.

Keep out of reach of children.

Overdose warning:

Taking more than directed can cause serious health problems. In case of overdose, get medical help or contact a Poison Control Center right away.1-800-222-1222

Directions

- take only one dose per day (24 hours) – see Overdose warning
- Measure with dosing cup provided.

adults & children 12 yrs & over | One Dose = 30 mL (2 tablespoons) at bed time if needed or as directed by a doctor
Children under 12 yrs | Do not use

Other information

- each 30 mL dose contains: sodium 23 mg
- store at room temperature
- protect from light. Does not meet USP <671>

Inactive ingredients

anhydrous citric acid, FD&C blue 1, FD&C red 40, flavor, glycerin, potassium citrate, purified water, sodium benzoate, sorbitol, sucralose, xanthan gum.

Questions or comments?

1-866-467-2748

PRINCIPAL DISPLAY PANEL

LEADER

NDC 70000-0174-1

Nighttime Sleep-aid

Diphenhydramine HCl

COMPARE TO ZZZQUIL®active ingredient*

100% money Back Guarantee

- Non-habit forming

Berry flavor

Naturally & Artificially Flavored

- Non-habit forming

12 FL OZ (354 mL)

©2016 Cardinal Health, All Rights Reserved CARDINAL HEALTH, the Cardinal Health LOGO,LEADER, and the Leader LOGO are trademarks or registered trademarks of Cardinal health.

Failure to follow these warnings could result in serious consequences.

TAMPER EVIDENT: Do not use if printed shrink band is missing or broken

DISTRIBUTED BY: CARDINAL HEALTH

DUBLIN,OHIO 43017

www.myleader.com1-800-200-6313

*This product is not manufactured or distributed by Procter & Gamble, the owner of the registered trademark ZzzQuil®.